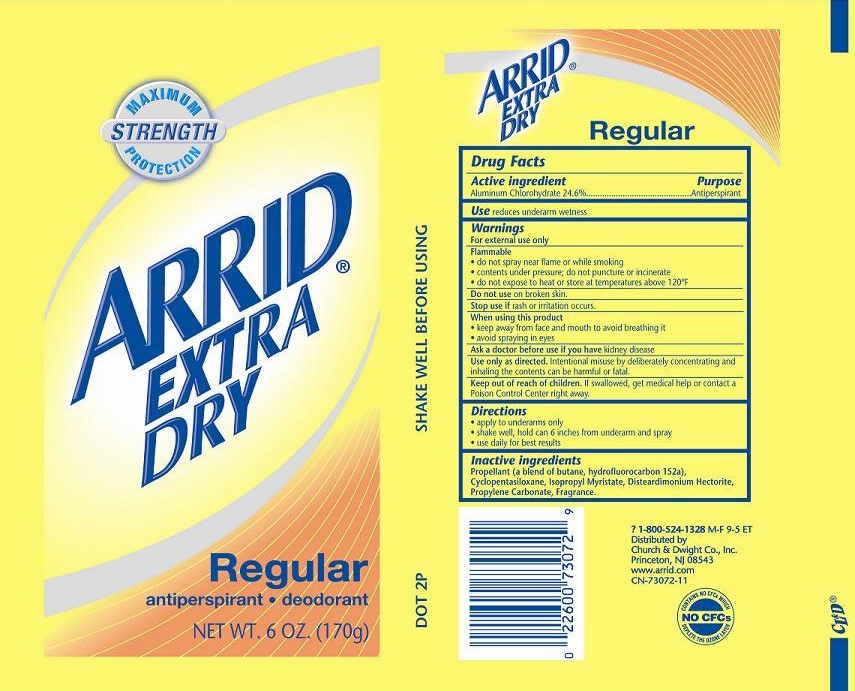 DRUG LABEL: ARRID EXTRA DRY
NDC: 10237-814 | Form: AEROSOL, SPRAY
Manufacturer: Church & Dwight Co., Inc.
Category: otc | Type: HUMAN OTC DRUG LABEL
Date: 20251212

ACTIVE INGREDIENTS: ALUMINUM CHLOROHYDRATE 246 mg/1 g
INACTIVE INGREDIENTS: BUTANE; 1,1-DIFLUOROETHANE; CYCLOMETHICONE 5; ISOPROPYL MYRISTATE; HECTORITE; PROPYLENE CARBONATE

Arrid Extra Dry Regular Aerosol

Active Ingredient

Aluminum Chlorohydrate 24.6%

Purpose

Antiperspirant

Use

reduces underarm wetness

Warnings

For external use only

Flammable

- do not spray near flame or while smoking
- contents under pressure do not puncture or incinerate
- do not expose to heat or store at temperatures above 120ºF

Use only as directed. Intentional misuse by deliberately concentrating and inhaling the contents can be harmful or fatal.

Do not use on broken skin.

Stop use if rash or irritation occurs.

When using this product

- keep away from face and mouth to avoid breathing it
- avoid spraying in eyes

Keep out of reach of children. If swallowed, get medical help or contact a Poison Control Center right away.

Ask a doctor before use if you have kidney disease.

Directions

- apply to underarms only
- shake well, hold can 6 inches from underarm and spray
- use daily for best results

Inactive ingredients

Propellant (a blend of butane, hydrofluorocarbon 152a), Cyclopentasiloxane, Isopropyl Myristate, Disteardimonium Hectorite, Propylene Carbonate, Fragrance.

Principal Display Panel

MAXIMUM STRENGTH PROTECTION

ARRID EXTRA DRY

Regular

AEROSOL

antiperspirant • deodorant

NEW WT. 6.0 OZ. (170g)